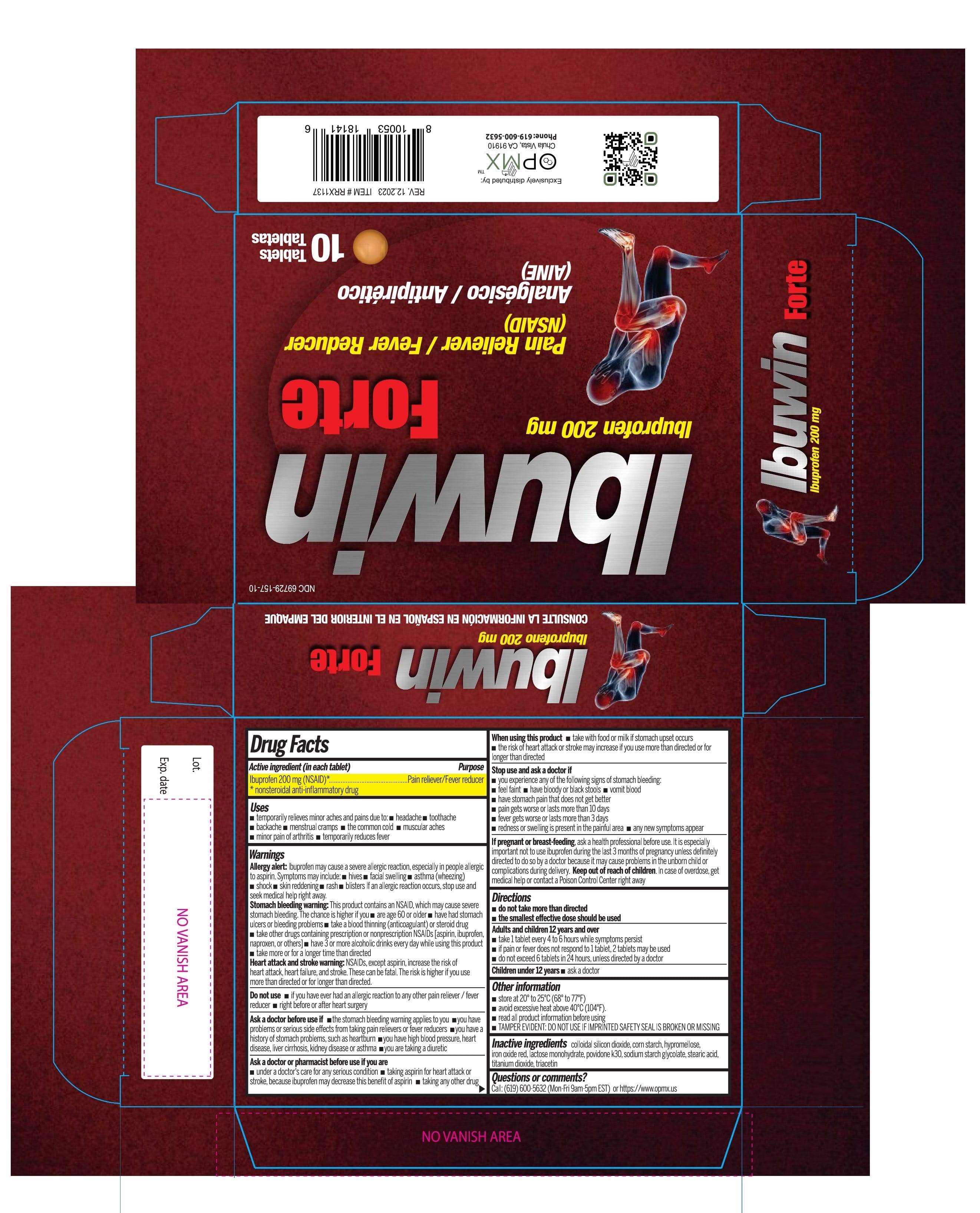 DRUG LABEL: Ibuwin Forte
NDC: 69729-157 | Form: TABLET
Manufacturer: OPMX LLC
Category: otc | Type: HUMAN OTC DRUG LABEL
Date: 20231229

ACTIVE INGREDIENTS: IBUPROFEN 200 mg/1 1
INACTIVE INGREDIENTS: STARCH, CORN; POVIDONE K30; STEARIC ACID; SILICON DIOXIDE; SODIUM STARCH GLYCOLATE TYPE A POTATO; TITANIUM DIOXIDE; FERRIC OXIDE RED; HYPROMELLOSE, UNSPECIFIED; TRIACETIN; LACTOSE MONOHYDRATE

Ibuwin Forte

Drug Facts

ACTIVE INGREDIENT (in each tablet/caplet)

Ibuprofen 200 mg (NSAID) *

nonsteroidal anti-inflammatory drug

PURPOSE

Pain reliever/Fever reducer

USES

- temporarily relieves minor aches and pains due to:
  - headache
  - toothache
  - backache
  - menstrual cramps
  - the common cold
  - muscular aches
  - minor pain of arthritis
- temporarily reduces fever

WARNINGS

Allergy alert: Ibuprofen may cause a severe allergic reaction, especially in people allergic to aspirin.
Symptoms may include:

- hives
- facial swelling
- asthma (wheezing)
- shock
- skin reddening
- rash
- blisters

If an allergic reaction occurs, stop use and seek medical help right away.

Stomach bleeding warning

This product contains an NSAID, which may cause severe stomach bleeding.

The chance is higher if you:

- are age 60 or older
- have had stomach ulcers or bleeding problems
- take a blood thinning (anticoagulant) or steroid drug
- take other drugs containing prescription or nonprescription NSAIDs [aspirin, ibuprofen, naproxen, or others]
- have 3 or more alcoholic drinks every day while using this product
- take more or for a longer time than directed

Heart attack and stroke warning
NSAIDs, except aspirin, increase the risk of heart attack, heart failure, and stroke. These can be fatal. The risk is higher if you use more than directed or for longer than directed.

DO NOT USE

- if you have ever had an allergic reaction to any other pain reliever/fever reducer
- right before or after heart surgery

ASK A DOCTOR BEFORE USE IF

- the stomach bleeding warning applies to you
- you have problems or serious side effects from taking pain relievers or fever reducers
- you have a history of stomach problems, such as heartburn
- you have high blood pressure, heart disease, liver cirrhosis, kidney disease or asthma
- you are taking a diuretic

ASK A DOCTOR OR PHARMACIST BEFORE USE IF YOU ARE

- under a doctor’s care for any serious condition
- taking aspirin for heart attack or stroke, because ibuprofen may decrease this benefit of aspirin
- taking any other drug

WHEN USING THIS PRODUCT

- take with food or milk if stomach upset occurs
- the risk of heart attack may increase if you use more than directed or for longer than directed

STOP USE AND ASK A DOCTOR IF

- you experience any of the following signs of stomach bleeding:
- feel faint
- have bloody or black stools
- vomit blood
- have stomach pain that does not get better
- pain gets worse or lasts more than 10 days
- fever gets worse or lasts more than 3 days
- redness or swelling is present in the painful area
- any new symptoms appear

IF PREGNANT OR BREAST FEEDING,

ask a health professional before use. It is especially important not to use ibuprofen during the last 3 months of pregnancy unless definitely directed to do so by a doctor because it may cause problems in the unborn child or complications during delivery.

KEEP OUT OF REACH OF CHILDREN

In case of overdose, get medical help or contact a Poison Control Center right away.

DIRECTIONS

- do not take more than directed
- the smallest effective dose should be used
  adults and children 12 years and older | - take 1 caplet every 4 to 6 hours while symptoms persist - if pain or fever does not respond to 1 caplet, 2 caplets may be used - do not exceed 6 caplets in 24 hours, unless directed by a doctor
  children under 12 years | - ask a doctor

OTHER INFORMATION

- store at 20-25°C (68-77°F)
- avoid high humidity and excessive heat above 40°C (104°F)
- read all product information before using
- TAMPER EVIDENT: DO NOT USE IF IMPRINTED SAFETY SEAL IS BROKEN OR MISSING

INACTIVE INGREDIENTS

colloidal silicon dioxide, corn starch, hypromellose, iron oxide red, lactose monohydrate, povidone k-30, sodium starch glycolate, stearic acid, titanium dioxide, triacetin

QUESTIONS OR COMMENTS?

Call: (619) 600-5632 (Mon-Fri 9am-5pm EST) or https://www.opmx.us

PACKAGE LABEL.PRINCIPAL DISPLAY PANEL

NDC 69729-157-10

Ibuwin Forte

Ibuprofen 200 mg

Pain Reliever/Fever Reducer (NSAID)

Analgésico/Antipirético (AINE)

10 Tablets/Tabletas